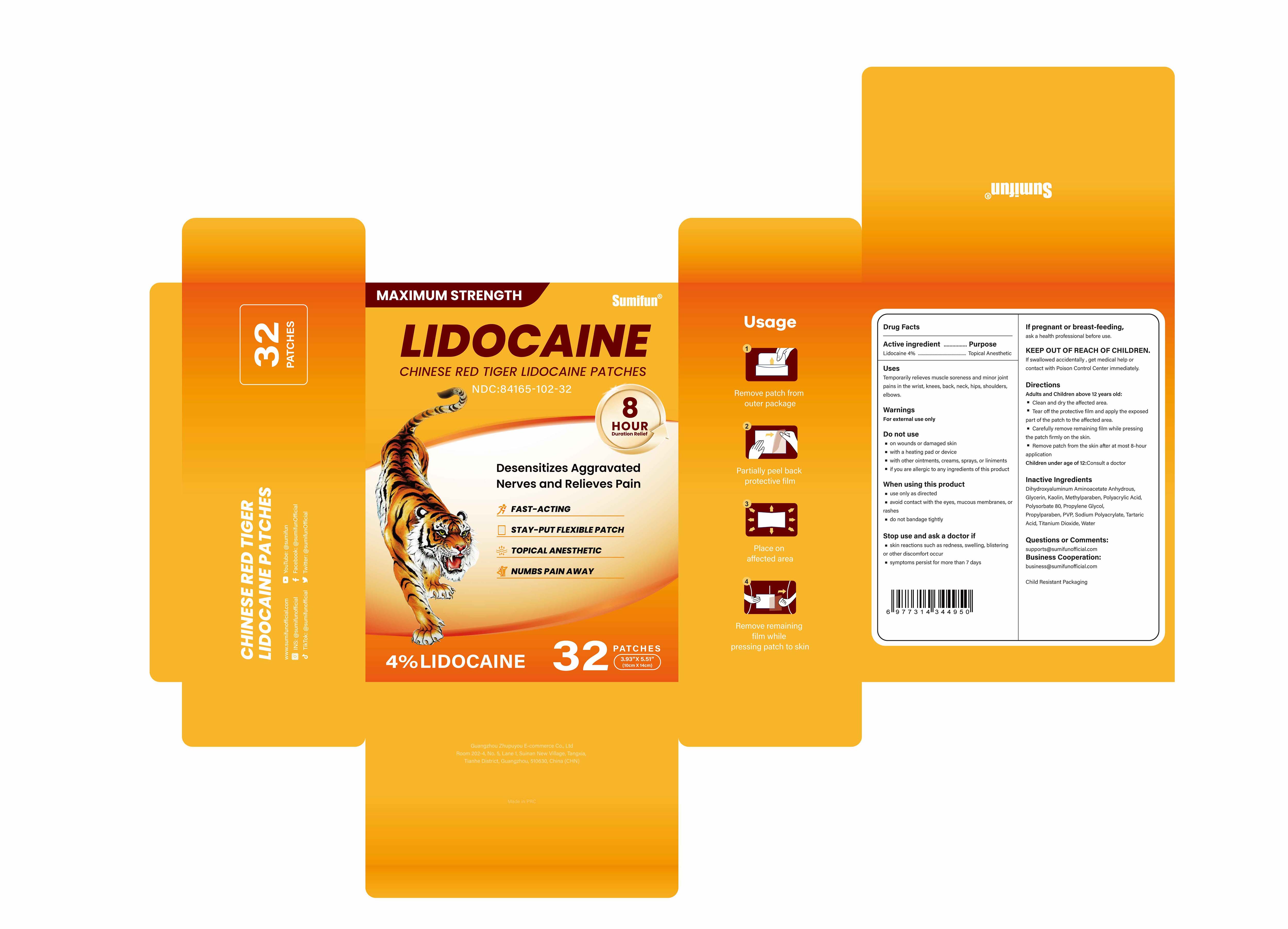 DRUG LABEL: Chinese Red Tiger Lidocaine Patches
NDC: 84165-102 | Form: PATCH
Manufacturer: Guangzhou Zhupuyou E-commerce Co., Ltd
Category: otc | Type: HUMAN OTC DRUG LABEL
Date: 20250810

ACTIVE INGREDIENTS: LIDOCAINE 0.04 g/1 g
INACTIVE INGREDIENTS: METHYLPARABEN; TARTARIC ACID; DIHYDROXYALUMINUM AMINOACETATE ANHYDROUS; SODIUM POLYACRYLATE (2500000 MW); KAOLIN; PROPYLENE GLYCOL; PROPYLPARABEN; GLYCERIN; WATER; POVIDONE K90; TITANIUM DIOXIDE; POLYACRYLIC ACID (250000 MW); POLYSORBATE 80

84165-102 Chinese Red Tiger Lidocaine Patches

Chinese Red Tiger Lidocaine Patches

ACTIVE INGREDIENT

Lidocaine 4%

PURPOSE

Topical Anesthetic

INDICATIONS AND USAGE

Temporarily relieves muscle soreness and minor jointpains in the wrist, knees, back, neck, hips, shoulders,elbows.

WARNINGS

For external use only

DO NOT USE

on wounds or damaged skin
with a heating pad or device
with other ointments, creams, sprays, or liniments
if you are allergic to any ingredients of this product

WHEN USING

use only as directed
avoid contact with the eyes, mucous membranes, orrashes
do not bandage tightly

STOP USE

skin reactions such as redness, swelling, blisteringor other discomfort occur
symptoms persist for more than 7 days

KEEP OUT OF REACH OF CHILDREN

If swallowed accidentally , get medical help orcontact with Poison Control Center immediately.

DOSAGE AND ADMINISTRATION

Clean and dry the affected area.
Tear off the protective film and apply the exposedpart of the patch to the affected area.
Carefully remove remaining film while pressingthe patch firmly on the skin.
Remove patch from the skin after at most 8-hourapplication
Children under age of 12:Consult a doctor

INACTIVE INGREDIENT

Dihydroxyaluminum Aminoacetate Anhydrous
Glycerin
Kaolin
Methylparaben
Polyacrylic Acid
Polysorbate 80
Propylene Glycol
Propylparaben
PVP
Sodium Polyacrylate
Tartaric Acid
Titanium Dioxide
Water